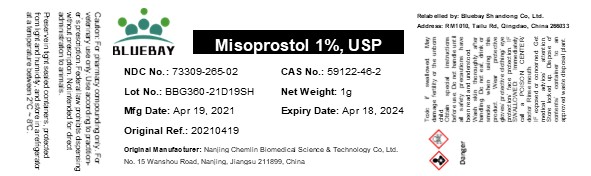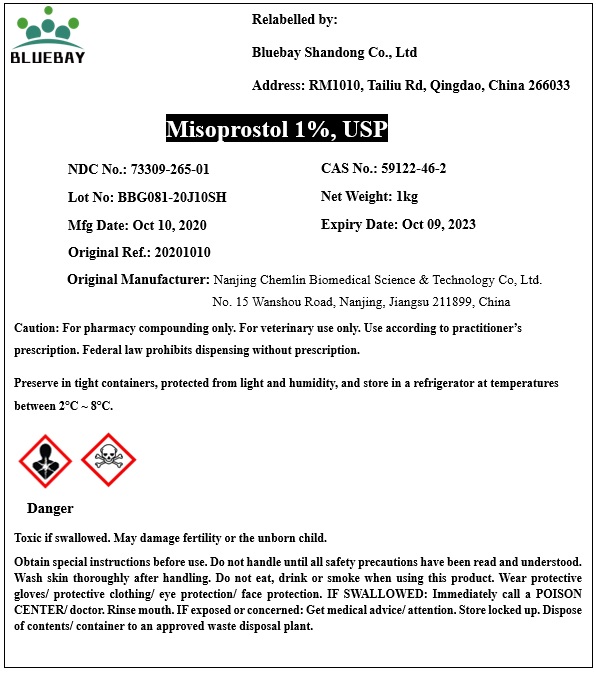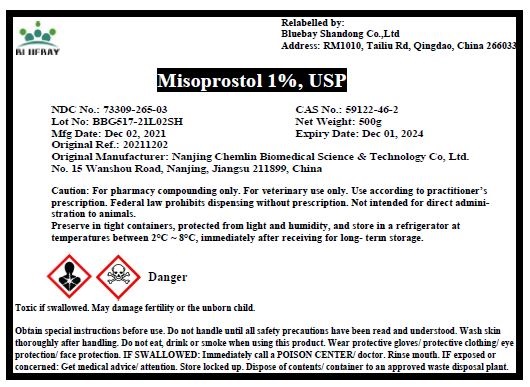 DRUG LABEL: Misoprostol 1%
NDC: 73309-265 | Form: POWDER
Manufacturer: BLUEBAY SHANDONG CO.,LTD
Category: other | Type: BULK INGREDIENT
Date: 20211217

ACTIVE INGREDIENTS: MISOPROSTOL 0.01 kg/1 kg

Misoprostol 1%